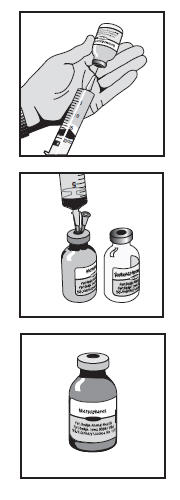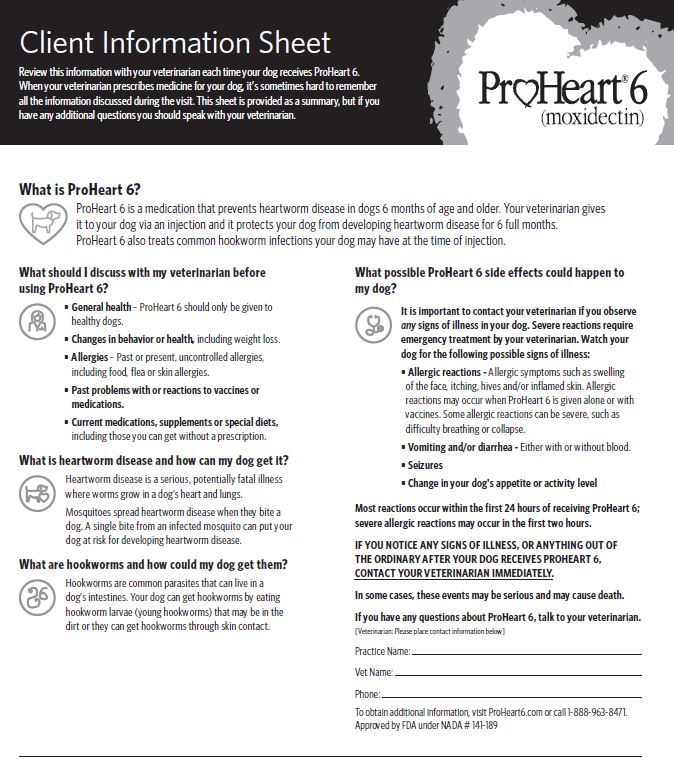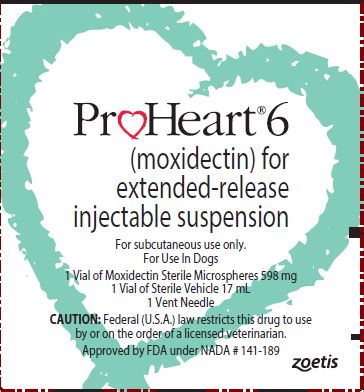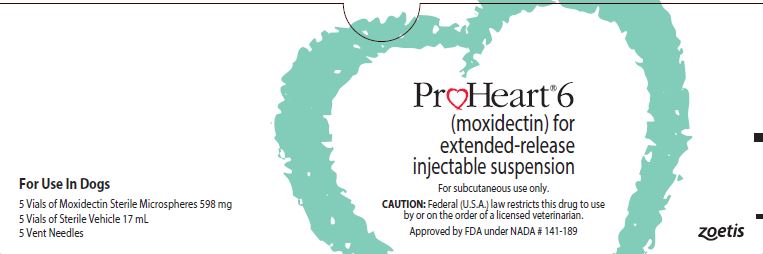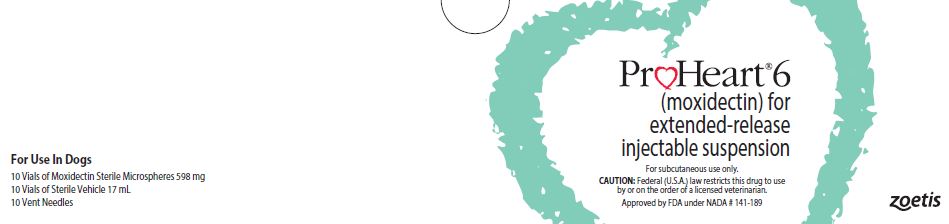 DRUG LABEL: ProHeart 6
NDC: 54771-3670 | Form: KIT | Route: SUBCUTANEOUS
Manufacturer: Zoetis Inc.
Category: animal | Type: PRESCRIPTION ANIMAL DRUG LABEL
Date: 20220323

ACTIVE INGREDIENTS: MOXIDECTIN 3.4 mg/1 mL
INACTIVE INGREDIENTS: TRISTEARIN; BUTYLATED HYDROXYTOLUENE; HYPROMELLOSES; SODIUM CHLORIDE

ProHeart® 6 (moxidectin)
For Extended-Release Injectable Suspension for Dogs

CAUTION

Federal (U.S.A.) law restricts this drug to use by or on the order of a licensed veterinarian.

DESCRIPTION

ProHeart 6 (moxidectin) for extended-release injectable suspension consists of two separate vials: One vial contains 10% moxidectin sterile microspheres and the second vial contains a specifically formulated sterile vehicle for constitution with the microspheres. No other diluent should be used. A clear or translucent appearance of the vehicle is normal. Each mL of constituted drug product contains 3.4 mg moxidectin, 3.1% glyceryl tristearate, 2.4% hydroxypropyl methylcellulose, 0.87% sodium chloride, 0.17% methylparaben, 0.02% propylparaben and 0.001% butylated hydroxytoluene. Hydrochloric acid is used to adjust pH. The constituted product may appear as a hazy to milky suspension.

INDICATIONS

ProHeart 6 is indicated for use in dogs six months of age and older for the prevention of heartworm disease caused by Dirofilaria immitis for 6 months.
ProHeart 6 is indicated for the treatment of existing larval and adult hookworm (Ancylostoma caninum and Uncinaria stenocephala) infections.

DOSAGE AND ADMINISTRATION

Always provide Client Information Sheet and review with owners before administering ProHeart 6. The owner should be advised to observe their dog for adverse drug events including those described on the sheet.

Frequency of Treatment

ProHeart 6 prevents the development of heartworm disease caused by D. immitis for six months. It should be administered within one month of the dog’s first exposure to mosquitoes. Follow-up treatments may be given every six months if the dog has continued exposure to mosquitoes and if the dog continues to be healthy without weight loss. When replacing another heartworm preventive product, ProHeart 6 should be given within one month of the last dose of the former medication.
ProHeart 6 eliminates the larval and adult stages of A. caninum and U. stenocephala present at the time of treatment. However, persistent effectiveness has not been established for this indication. Re-infection with A. caninum and U. stenocephala may occur sooner than 6 months.

Dose

The recommended subcutaneous dose is 0.05 mL of the constituted suspension/kg body weight (0.0227 mL/lb.). This amount of suspension will provide 0.17 mg moxidectin/ kg bodyweight (0.0773 mg/lb.).
To ensure accurate dosing, calculate each dose based on the dog’s weight at the time of treatment. Do not overdose growing puppies in anticipation of their expected adult weight. The following dosage chart may be used as a guide.

DOSAGE CHART
Dog Wt. |  | Dose Volume | Dog Wt. |  | Dose Volume
lb | kg | mL/Dog | lb | kg | mL/Dog
11 | 5 | 0.25 | 77 | 35 | 1.75
22 | 10 | 0.50 | 88 | 40 | 2.00
33 | 15 | 0.75 | 99 | 45 | 2.25
44 | 20 | 1.00 | 110 | 50 | 2.50
55 | 25 | 1.25 | 121 | 55 | 2.75
66 | 30 | 1.50 | 132 | 60 | 3.00

Injection Technique

The two-part sustained release product must be mixed at least 30 minutes prior to the intended time of use (see CONSTITUTION PROCEDURES for initial mixing instructions). Once constituted, swirl the bottle gently before every use to uniformly re-suspend the microspheres. Withdraw 0.05 mL of suspension/kg body weight into an appropriately sized syringe fitted with an 18G or 20G hypodermic needle. Dose promptly after drawing into dosing syringe. If administration is delayed, gently roll the dosing syringe prior to injection to maintain a uniform suspension and accurate dosing.
Using aseptic technique, inject the product subcutaneously in the left or right side of the dorsum of the neck cranial to the scapula. No more than 3 mL should be administered in a single site. The location(s) of each injection (left or right side) should be noted so that prior injection sites can be identified and the next injection can be administered on the opposite side.

RISK MINIMIZATION ACTION PLAN

The ProHeart 6 and ProHeart 12 Risk Minimization Action Plan (RiskMAP) provides educational materials to the veterinarian, veterinary staff, and the dog owner explaining the risks and proper use of ProHeart 6 and ProHeart 12. ProHeart 6 and ProHeart 12 are the same formulation, but ProHeart 6 is three times less concentrated than ProHeart 12. ProHeart 6 and ProHeart 12 are for use in dogs only and are available through a restricted distribution program to veterinarians that have completed the RiskMAP training and certification module.

The ProHeart 6 and ProHeart 12 web-based training and certification module is available at http://www.proheart6.com. This website has important information on the safe and effective use of ProHeart 6 and ProHeart 12 for veterinarians.
Only veterinarians and veterinary technicians/assistants that have completed the training and are certified can administer ProHeart 6 and ProHeart 12. Veterinarians are expected to report all adverse events that occur in animals or humans to the manufacturer. Important safety information is included below:

CONTRAINDICATIONS

ProHeart 6 is contraindicated in animals previously found to be hypersensitive to this drug or ProHeart 12.

HUMAN WARNINGS

Not for human use. Keep this and all drugs out of the reach of children.

May be slightly irritating to the eyes. May cause slight irritation to the upper respiratory tract if inhaled. May be harmful if swallowed. If contact with the eyes
occurs, rinse thoroughly with water for 15 minutes and seek medical attention immediately. If accidental ingestion occurs, contact a Poison Control Center
or a physician immediately. The Safety Data Sheet (SDS) contains more detailed occupational safety information.

WARNINGS

Anaphylactic and anaphylactoid reactions may occur in some dogs following administration of ProHeart 6 alone or with vaccines. In some cases, these reactions have resulted in death following administration of moxidectin microspheres (see POST-APPROVAL EXPERIENCE). Anaphylactic and anaphylactoid reactions should be treated immediately with the same measures used to treat hypersensitivity reactions to vaccines and other injectable products.
Always provide Client Information Sheet and review with owners before administering ProHeart 6. The owner should be advised to observe their dog for adverse drug events including those described on the sheet.
Do not administer ProHeart 6 to dogs who are sick, debilitated, underweight or who have a history of weight loss.

PRECAUTIONS

Prior to administration of ProHeart 6, the health of the patient should be assessed by a thorough medical history, physical examination and diagnostic testing as indicated (see WARNINGS).
Caution should be used when administering ProHeart 6 in dogs with pre-existing allergic disease, including food allergy, atopy, and flea allergy dermatitis. (see WARNINGS).
Caution should be used when administering ProHeart 6 concurrently with vaccinations. Adverse reactions, including anaphylaxis, have been reported following the concomitant use of moxidectin microspheres and vaccinations (see WARNINGS and POST-APPROVAL EXPERIENCE).
ProHeart 6 should not be used more frequently than every 6 months.
The effectiveness of ProHeart 6 has not been evaluated in dogs less than 6 months of age.
Prior to administration of ProHeart 6, dogs should be tested for existing heartworm infections. Infected dogs should be treated with an adulticide to remove adult heartworms. ProHeart 6 is not effective against adult D. immitis.
Caution should be used when administering ProHeart 6 to heartworm positive dogs (see ADVERSE REACTIONS).

ADVERSE REACTIONS

In field studies, the following adverse reactions were observed in dogs treated with ProHeart 6: anaphylaxis, vomiting, diarrhea (with and without blood), listlessness, weight loss, seizures, injection site pruritus, and elevated body temperature. Dogs with clinically significant weight loss (>10%) were more likely to experience a severe adverse reaction.

In a laboratory effectiveness study, dogs with 4- and 6-month-old heartworm infections experienced vomiting, lethargy and bloody diarrhea. These signs were more severe in the dogs with 4-month-old heartworm infections, including one dog that was recumbent and required supportive care, than in the dogs with older (6-month-old) infections.

Post-Approval Experience (Rev. 2018)

The following adverse events are based on post-approval adverse drug experience reporting. Not all adverse reactions are reported to FDA/CVM. It is not always possible to reliably estimate the adverse event frequency or establish a causal relationship to product exposure using these data. The following adverse events are listed in decreasing order of frequency by body system.

Immune: anaphylaxis and/or anaphylactoid reactions, urticaria, head/facial edema, pruritus, pale mucous membranes, collapse, cardiovascular shock, erythema, immune-mediated hemolytic anemia, immune-mediated thrombocytopenia (signs reflected in other system categories could be related to allergic reactions, i.e. gastrointestinal, dermatologic, and hematologic)

Gastrointestinal: vomiting (with or without blood), diarrhea with or without blood, hypersalivation

General: depression, lethargy, anorexia, fever, weight loss, weakness

Dermatological: injection site pruritus/swelling, erythema multiforme

Neurological: seizures, ataxia, trembling, hind limb paresis

Hematological: leukocytosis, anemia, thrombocytopenia

Respiratory: dyspnea, tachypnea, coughing

Hepatic: elevated liver enzymes, hypoproteinemia, hyperbilirubinemia, hepatopathy

Urinary: elevated BUN, elevated creatinine, hematuria, polydipsia, polyuria

Cardiopulmonary signs such as coughing and dyspnea may occur in heartworm positive dogs.
In some cases, death has been reported as an outcome of the adverse events listed above.
For a copy of the Safety Data Sheet (SDS) or to report suspected adverse reactions, contact Zoetis at 1-888-963-8471. For additional information about adverse drug experience reporting for animal drugs, contact FDA at 1-888-FDA-VETS or www.fda.gov/reportanimalae.

INFORMATION FOR DOG OWNERS

Always provide Client Information Sheet and review with owners before administering ProHeart 6. Owners should be advised of the potential for adverse reactions, including anaphylaxis, and be informed of the clinical signs associated with drug toxicity (see WARNINGS, ADVERSE REACTIONS and POST-APPROVAL EXPERIENCE sections.)
Owners should be advised to contact their veterinarian immediately if signs of toxicity are observed. The vast majority of patients with drug related adverse reactions have recovered when the signs are recognized and veterinary care, if appropriate, is initiated.

CLINICAL PHARMACOLOGY

Moxidectin is a semi-synthetic methoxime derivative of nemadectin which is a fermentation product of Streptomyces cyaneogriseus subspecies noncyanogenus. Moxidectin is a pentacyclic 16-membered lactone macrolide.

Moxidectin has activity resulting in paralysis and death of affected parasites. The stage of the canine heartworm affected at the recommended dose rate of 0.5 mg/kg (0.227 mg/lb) is the tissue larval stage.
The larval and adult stages of the canine hookworms, A. caninum and U. stenocephala, are susceptible.
Following injection with ProHeart 6, peak moxidectin blood levels will be observed approximately 7-14 days after treatment. At the end of the 6-month dosing interval, residual drug plasma concentrations are negligible. Accordingly, little or no drug accumulation is expected to occur with repeated administrations.

ANIMAL SAFETY

General Safety: ProHeart 6 has been administered to a wide variety of healthy dogs six months of age and older, including a wide variety of breeds, pregnant and lactating females, breeding males, and ivermectin-sensitive collies. In clinical studies, two geriatric dogs with a history of weight loss after the initial ProHeart 6 injection died within a month of the second 6 month injection. A third dog who was underweight for its age and breed and who had a history of congenital problems experienced lethargy following the initial injection of ProHeart 6. The dog never recovered and died 3 months later (see WARNINGS).

ProHeart 6 administered at 3 times the recommended dose in dogs with patent heartworm infections and up to 5 times the recommended dose in ivermectin-sensitive collies did not cause any adverse reactions. ProHeart 6 administered at 3 times the recommended dose did not adversely affect the reproductive performance of male or female dogs.

ProHeart 6 administered up to 5 times the recommended dose in 7-8 month old puppies did not cause any systemic adverse effects.

In well controlled clinical field studies, ProHeart 6 was used in conjunction with a variety of veterinary products including anthelmintics, antiparasitics, antibiotics, analgesics, steroids, non-steroidal anti-inflammatory drugs (NSAIDs), anesthetics and flea control products.

Injection Site Reactions: Injection site observations were recorded during effectiveness and safety studies. In clinical studies, ProHeart 6 was administered at six-month intervals to client-owned dogs under field conditions. There were no reports of injection site reactions in these field studies and evaluations of the injection sites revealed no abnormalities.

In a laboratory safety study, ProHeart 6 was administered at 1, 3 and 5 times the recommended dose to 7-8 month old puppies. Injection sites were clipped to facilitate observation. Slight swelling/edema at the injection site was observed in some dogs from all treated groups. These injection site reactions appeared as quickly as 8 hours post injection and lasted up to 3 weeks. A three-year repeated injection study was conducted to evaluate the safety of up to 6 injections of ProHeart 6 administered at the recommended dose (0.17 mg/kg) every 6 months. Mild erythema and localized deep subcuticular thickening were seen in dogs that received four injections in the same area on the neck and in one dog that received two injections in the same area on the neck. Microscopic evaluation on the injection sites from all dogs 6 months after the last injection consistently showed mild granulomatous panniculitis with microvacuolation. The only adverse reaction seen that was not related to the injection site was weight loss in one dog.

Some dogs treated with ProHeart 6 in laboratory effectiveness studies developed transient, localized inflammatory injection site reactions. These injection site reactions were visible grossly for up to 3 weeks after injection. Histologically, well-defined granulomas were observed in some dogs at approximately 5 months after injection.

CONSTITUTION PROCEDURES

The two-part ProHeart 6 product must be mixed at least 30 minutes prior to the intended time of use.

Items needed to constitute ProHeart 6: | - Microspheres - Sterile 20 mL syringe for transfer | - Enclosed vent needle (25G) - Transfer needle (18G or 20G) | - Sterile Vehicle

 | Constitution of the 20 mL vial product (17.7 mL when constituted).
 | 1. | Shake the microsphere vial to break up any aggregates prior to constitution.
 | 2. | Using an 18G or 20G needle and sterile syringe withdraw 17.0 mL of the unique sterile vehicle from the vial. There is more sterile vehicle supplied than the 17.0 mL required.
 | 3. | Insert the enclosed 25G vent needle into the microsphere vial.
 | 4. | Slowly transfer the sterile vehicle into the microsphere vial through the stopper using the transfer needle and syringe.
 | 5. | Once the sterile vehicle has been added, remove the vent and transfer needles from the microsphere vial. Discard unused sterile vehicle and needles.
 | 6. | Shake the microsphere vial vigorously until a thoroughly mixed suspension is produced. The constituted product may appear as a hazy to milky suspension.
 | 7. | Record the time and date of mixing on the microsphere vial.
 | 8. | Allow suspension to stand for at least 30 minutes to allow large air bubbles to dissipate.
 | 9. | Before every use, gently swirl the mixture to achieve uniform suspension. The constituted product may appear as a hazy to milky suspension. The microspheres and vehicle will gradually separate on standing.
 | 10. | Use a 1 mL or 3 mL syringe and an 18G or 20G needle for dosing. Dose promptly after drawing into dosing syringe. If administration is delayed, gently roll the dosing syringe prior to injection to maintain a uniform suspension and accurate dosing.
 | 11. | Refrigerate the unused product. The constituted product remains stable for 8 weeks in a refrigerator. Avoid direct sunlight.

STORAGE INFORMATION

Store the unconstituted product at or below 25°C (77°F). Do not expose to light for extended periods of time. After constitution, the product is stable for 8 weeks stored under refrigeration at 2° to 8°C (36° to 46°F).

HOW SUPPLIED

ProHeart 6 is available in the following three package sizes.

1. | 1-Pack |  | 2. | 5-Pack |  | 3. | 10-Pack
 | 20 mL vial product: |  |  | 20 mL vial product: |  |  | 20 mL vial product:
 | 1 - 10% moxidectin sterile microspheres |  |  | 5 - 10% moxidectin sterile microspheres |  |  | 10 - 10% moxidectin sterile microspheres
 | - 598 mg/vial |  |  | - 598 mg/vial |  |  | - 598 mg/vial
 | 1 - Sterile vehicle - 17 mL/vial |  |  | 5 - Sterile vehicle - 17 mL/vial |  |  | 10 - Sterile vehicle - 17 mL/vial

Client Information Sheet

Distributed by: Zoetis Inc. Kalamazoo, MI 49007
All trademarks are the property of Zoetis Services LLC or a related company or a licensor unless otherwise noted.
© 2020 Zoetis Services LLC. All rights reserved. PRO-00309
zoetis

zoetis

Distributed by Zoetis Inc., Kalamazoo, MI 49007

Approved by FDA under NADA # 141-189

Revised: November 2021
40036951